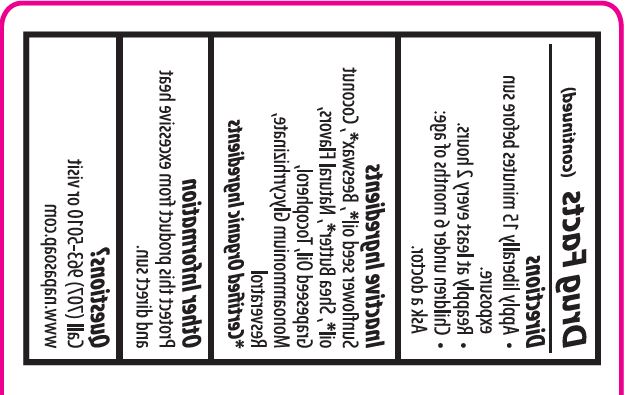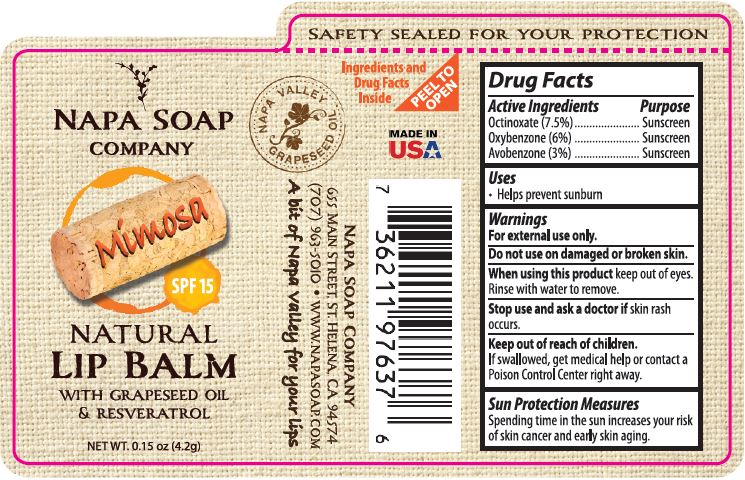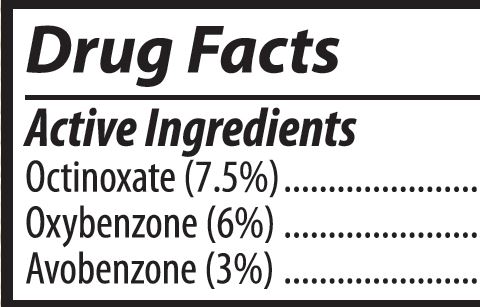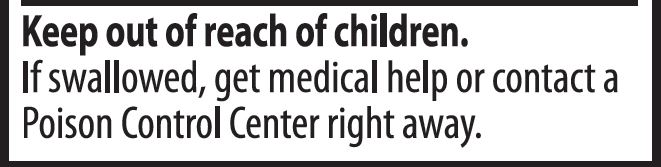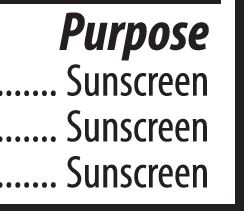 DRUG LABEL: LIP BALM
NDC: 62932-236 | Form: STICK
Manufacturer: Private Label Select Ltd CO
Category: otc | Type: HUMAN OTC DRUG LABEL
Date: 20201230

ACTIVE INGREDIENTS: OXYBENZONE 6 g/100 g; OCTINOXATE 7.5 g/100 g; AVOBENZONE 3 g/100 g
INACTIVE INGREDIENTS: SUNFLOWER OIL; WHITE WAX; GRAPE SEED OIL; COCONUT OIL; SHEA BUTTER; .ALPHA.-TOCOPHEROL, D-; RESVERATROL; TANGERINE; .BETA.-TOCOPHEROL; .DELTA.-TOCOPHEROL; .GAMMA.-TOCOPHEROL; AMMONIUM GLYCYRRHIZATE; ORANGE OIL

Napa Soap Mimosa SPF 15 Natural Lip Balm